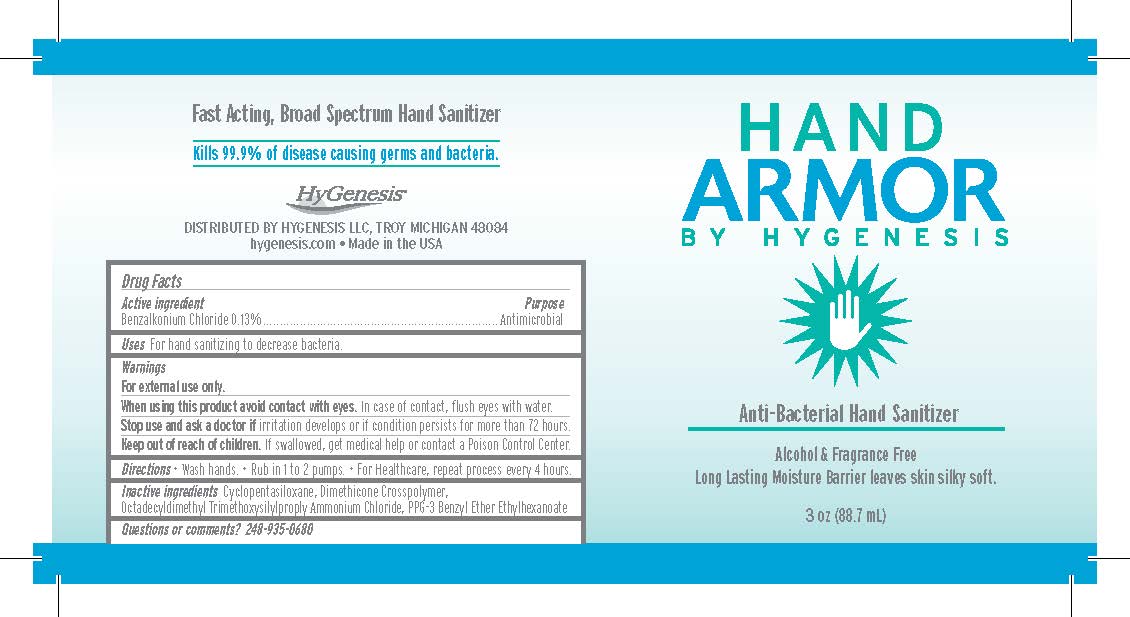 DRUG LABEL: Hand Armor
NDC: 58590-001 | Form: LIQUID
Manufacturer: HyGenesis
Category: otc | Type: HUMAN OTC DRUG LABEL
Date: 20211015

ACTIVE INGREDIENTS: BENZALKONIUM CHLORIDE 1.3 mg/1 g
INACTIVE INGREDIENTS: CYCLOMETHICONE 5; DIMETHYLOCTADECYL(3-(TRIMETHOXYSILYL)PROPYL)AMMONIUM CHLORIDE; PPG-3 BENZYL ETHER ETHYLHEXANOATE

Active ingredient

Benzalkonium Chloride 0.13%

Purpose

Antimicrobial

Uses

For hand sanitizing to decrease bacteria.

Warnings

For external use only.

When using this product avoid contact with eyes.

In case of contact, flush eyes with water.

Stop use and ask a doctor if

irritation develops or if condition persists for more than 72 hours.

Keep out of reach of children.

If swallowed, get medical help or contact a Poison Control Center.

Directions

- Wash hands
- Rub in 2 to 4 drops
- For Healthcare, repeat process every 4 hours

Inactive ingredients

Cyclopentasiloxane, Dimethicone Crosspolymer, Octadecyldimethyl Trimethoxysilylproply Ammonium Chloride, PPG-3 Benzyl Ether Ethylhexanoate

Questions or commetns?

248-342-8040